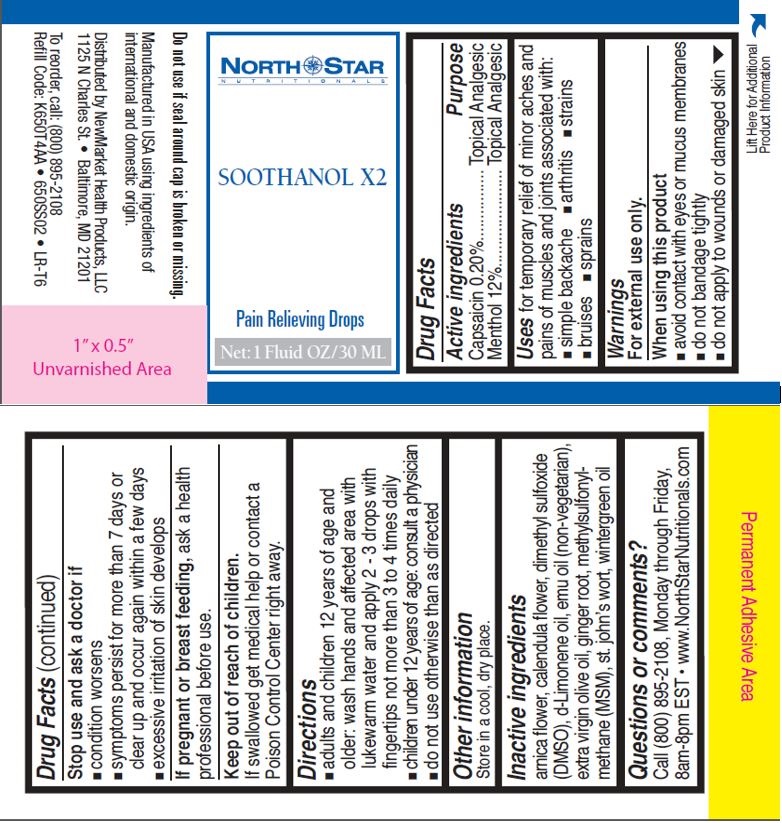 DRUG LABEL: Soothanol X2
NDC: 50972-766 | Form: SOLUTION/ DROPS
Manufacturer: NewMarket Health Products LLC
Category: otc | Type: HUMAN OTC DRUG LABEL
Date: 20170831

ACTIVE INGREDIENTS: CAPSAICIN 2 mg/1 g; MENTHOL 120 mg/1 g
INACTIVE INGREDIENTS: ARNICA ANGUSTIFOLIA FLOWER; CALENDULA OFFICINALIS FLOWER; DIMETHYL SULFOXIDE; LIMONENE, (+)-; EMU OIL; OLIVE OIL; GINGER; DIMETHYL SULFONE; ST. JOHN'S WORT; METHYL SALICYLATE

Soothanol X2

Active Ingredients

Capsaicin 0.20%

Menthol 12%

Purpose

Topical Analgesic

Topical Analgesic

INDICATIONS AND USAGE

Uses for temporary relief of minor aches and pains of muscles and joints associated with:

- simple backache
- arthritis
- strains
- bruises
- sprains

Warnings

For external use only.

When using this product

- avoid contact with eyes or mucus membranes
- do not bandage tighly
- do not apply to wounds or damaged skin

Stop use and ask doctor if

- condition worsens
- symptoms persist for more than 7 days or clear up and occur again within a few days
- excessive irritation of skin develops

PREGNANCY

If pregnant or breast feeding, ask a health professional before use.

Keep out of reach of children.

OTHER SAFETY INFORMATION

If swallowed get medical help or contact a Poison Control Center right away.

Directions

- adults and children 12 years of age and older: wash hands and affected area with lukewarm water and apply 2-3 drops with fingertips not more than 3 to 4 times daily
- children under 12 years of age: consult a physician
- do not use otherwise than as directed

Other information

Store in a cool, dry place.

Inactive ingredients

arnica flower, calendula flower, dimethyl sulfoxide (DMSO), d-Limonene oil, emu oil (non-vegetarian), extra virgin olive oil, ginger root, methylsulfonylmethane (MSM), st. john's wort, wintergreen oil

Questions or comments?

Call (800) 895-2108, Monday through Friday, 8am-8pm EST

www.NorthStarNutritionals.com

PACKAGE LABEL

North Star

Nutritionals

SOOTHANOL X2

Pain Relieving Drops

Net: 1 Fluid OZ/ 30 ML